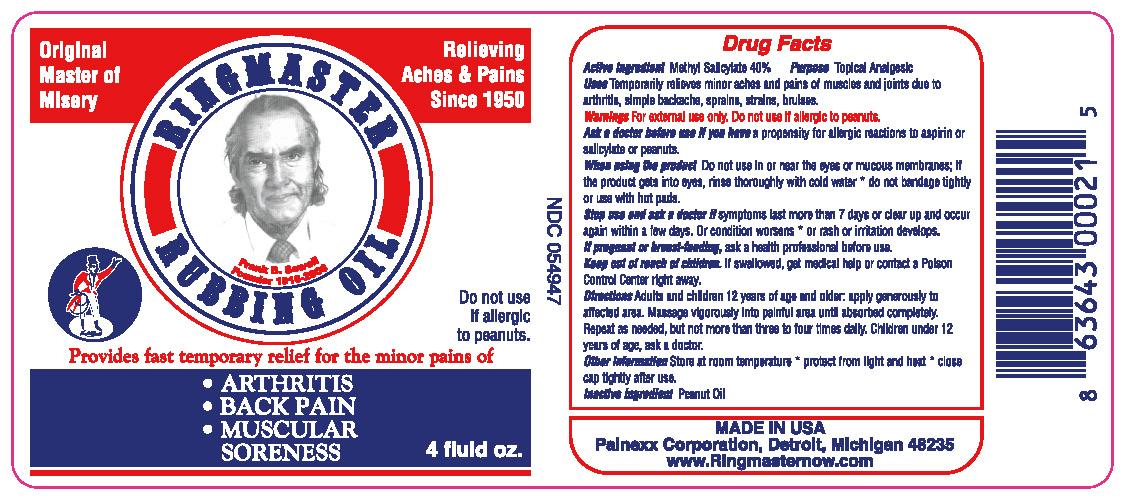 DRUG LABEL: Ringmaster Rubbing Oil
NDC: 54947-124 | Form: LIQUID
Manufacturer: Painexx Corporation
Category: otc | Type: HUMAN OTC DRUG LABEL
Date: 20180222

ACTIVE INGREDIENTS: METHYL SALICYLATE 40 g/100 mL
INACTIVE INGREDIENTS: PEANUT OIL

DOSAGE AND ADMINISTRATION

Rub every four hours as needed

Directions

For external use only. Do not use if allergic to peanuts

Inactive ingredient

Peanut Oil

Indications and usage

For the treatment of the minor aches and pains associated with arthritis

Keep out reach of children

Keep out of reach of children

Purpose

Topical analgesic

Active ingredient

Methyl Salicylate